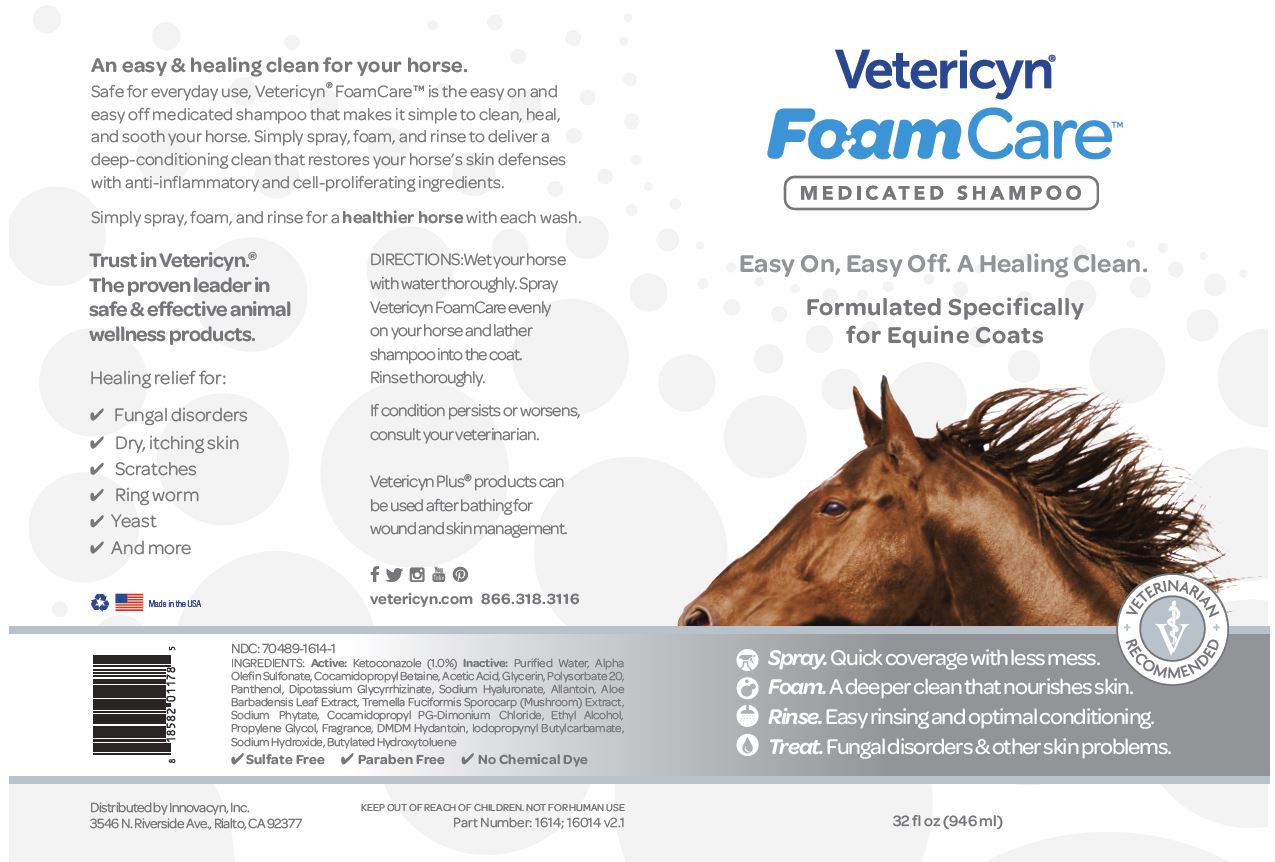 DRUG LABEL: Vetericyn FoamCare
NDC: 70489-1614 | Form: SHAMPOO
Manufacturer: Innovacyn Inc.
Category: animal | Type: OTC ANIMAL DRUG LABEL
Date: 20251218

ACTIVE INGREDIENTS: KETOCONAZOLE 10 mg/1 mL
INACTIVE INGREDIENTS: WATER; SODIUM C14-16 OLEFIN SULFONATE; COCAMIDOPROPYL BETAINE; ACETIC ACID; GLYCERIN ; POLYSORBATE 20; PANTHENOL ; ENOXOLONE DIPOTASSIUM; HYALURONATE SODIUM ; ALLANTOIN; ALOE VERA LEAF; TREMELLA FUCIFORMIS FRUITING BODY; PHYTATE SODIUM; COCAMIDOPROPYL PROPYLENE GLYCOL-DIMONIUM CHLORIDE; ALCOHOL; PROPYLENE GLYCOL; DMDM HYDANTOIN; IODOPROPYNYL BUTYLCARBAMATE; SODIUM HYDROXIDE; BUTYLATED HYDROXYTOLUENE

Package Labeling

ACTIVE INGREDIENT

NDC:70489-1614-1

INGREDIENTS:

Active: Ketoconazole (1.0%)

Inactive: Purified Water, Alpha Olefin Sulfonate, Cocamidopropyl Betaine, Acetic Acid, Glycerin, Polysorbate 20, Panthenol, Dipotassion Glycyrrhizinate, Sodium Hyaluronate, Allantoin, Aloe Barbadensis Leaf Extract, Tremella Fuciformis Sporocarp (Mushroom) Extract, Sodium Phytate, Cocamidopropyl PG-Dimonium Chloride, Ethyl Alcohol, Propylene Glycol, Fragrance, DMDM Hydantoin, Iodopropynyl Butylcarbamate, Sodium Hydroxide, Butylated Hydroxytoluene

Sulfate Free Paraben Free No Chemical dye

DESCRIPTION

An easy and healing clean for your horse.

Safe for everyday use, Vetericyn FoamCare is the easy on and easy off medicated shampoo that makes it simple to clean, heal, and sooth your horse. Simply spray,foam, and rinse to deliver a deep-conditioning clean that restores your horse's skin defenses with anti-inflammatory and cell-proliferating ingredients.

Simply spray, foam, and rinse for a healthier horse with each wash.

Trust in Vetericyn.The proven leader in safe and effective animal wellness products.

Healing relief for :

Fungal disorders

Dry, itching skin

Scratches

Ring Worm

Yeast

And more

Logo Recycle Logo U.S. Flag Made in the USA

DIRECTIONS:

Wet your horse with water thoroughly.

Spray Vetericyn FoamCare evenly on your horse and lather shampoo into the coat.

Rinse thoroughly.

GENERAL PRECAUTIONS

If condition persists or worsens, consult your veterinarian.

Vetericyn Plus products can be used after bathing for wound and skin management.

QUESTIONS

vetericyn.com 866.318.3116

KEEP OUT OF REACH OF CHILDREN.

NOT FOR HUMAN USE